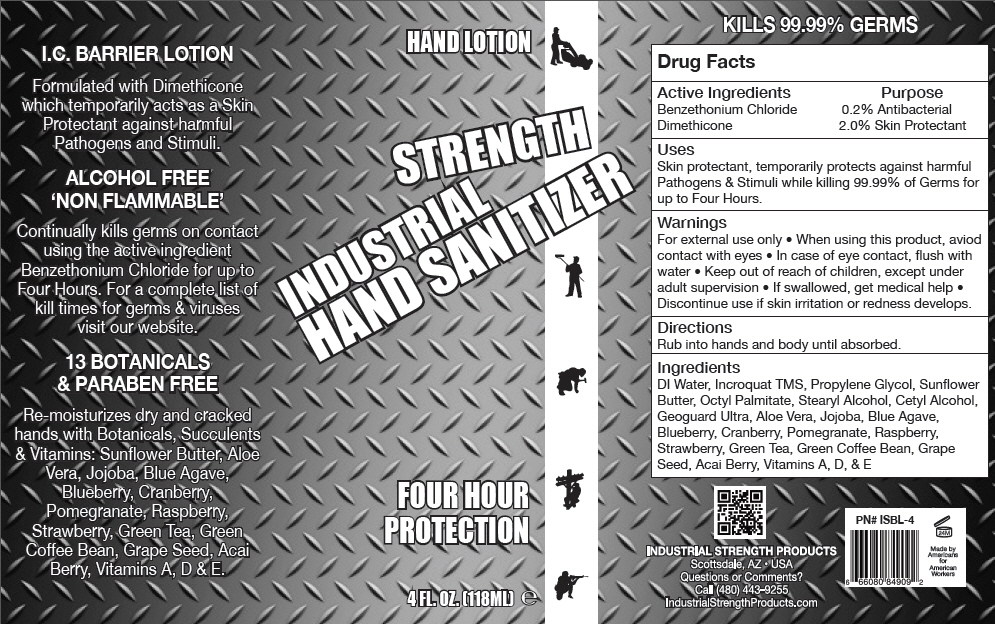 DRUG LABEL: Industrial Sanitizing
NDC: 59555-902 | Form: LOTION
Manufacturer: R&R Lotion, Inc.
Category: otc | Type: HUMAN OTC DRUG LABEL
Date: 20151208

ACTIVE INGREDIENTS: Benzethonium Chloride 2 mg/1 mL; Dimethicone 20 mg/1 mL
INACTIVE INGREDIENTS: Water; Propylene Glycol; Stearyl Alcohol; cholecalciferol; Cetyl Alcohol; vitamin A; Behentrimonium Methosulfate; Cetostearyl Alcohol; .Alpha.-Tocopherol; Ethylhexyl Palmitate; Gluconolactone; Sodium Benzoate; Calcium Gluconate

Industrial Sanitizing Lotion

Drug Facts

ACTIVE INGREDIENT

Active Ingredients | Purpose
Benzethonium Chloride 0.2% | Antibacterial
Dimethicone 2.0% | Skin Protectant

Uses

Skin protectant, temporarily protects against harmful Pathogens & Stimuli while killing 99.99% of Germs for up to Four Hours.

Warnings

For external use only

- When using this product, aviod contact with eyes
- In case of eye contact, flush with water

- Keep out of reach of children, except under adult supervision
- If swallowed, get medical help
- Discontinue use if skin irritation or redness develops.

Directions

Rub into hands and body until absorbed.

Ingredients

DI Water, Incroquat TMS, Propylene Glycol, Sunflower Butter, Octyl Palmitate, Stearyl Alcohol, Cetyl Alcohol, Geoguard Ultra, Aloe Vera, Jojoba, Blue Agave, Blueberry, Cranberry, Pomegranate, Raspberry, Strawberry, Green Tea, Green Coffee Bean, Grape Seed, Acai Berry, Vitamins A, D, & E

Questions or Comments?

Call (480) 443-9255

PRINCIPAL DISPLAY PANEL - 118 ML Bottle Label

HAND LOTION

STRENGTH

INDUSTRIAL
HAND SANITIZER

FOUR HOUR
PROTECTION

4 FL. OZ. (118ML) e